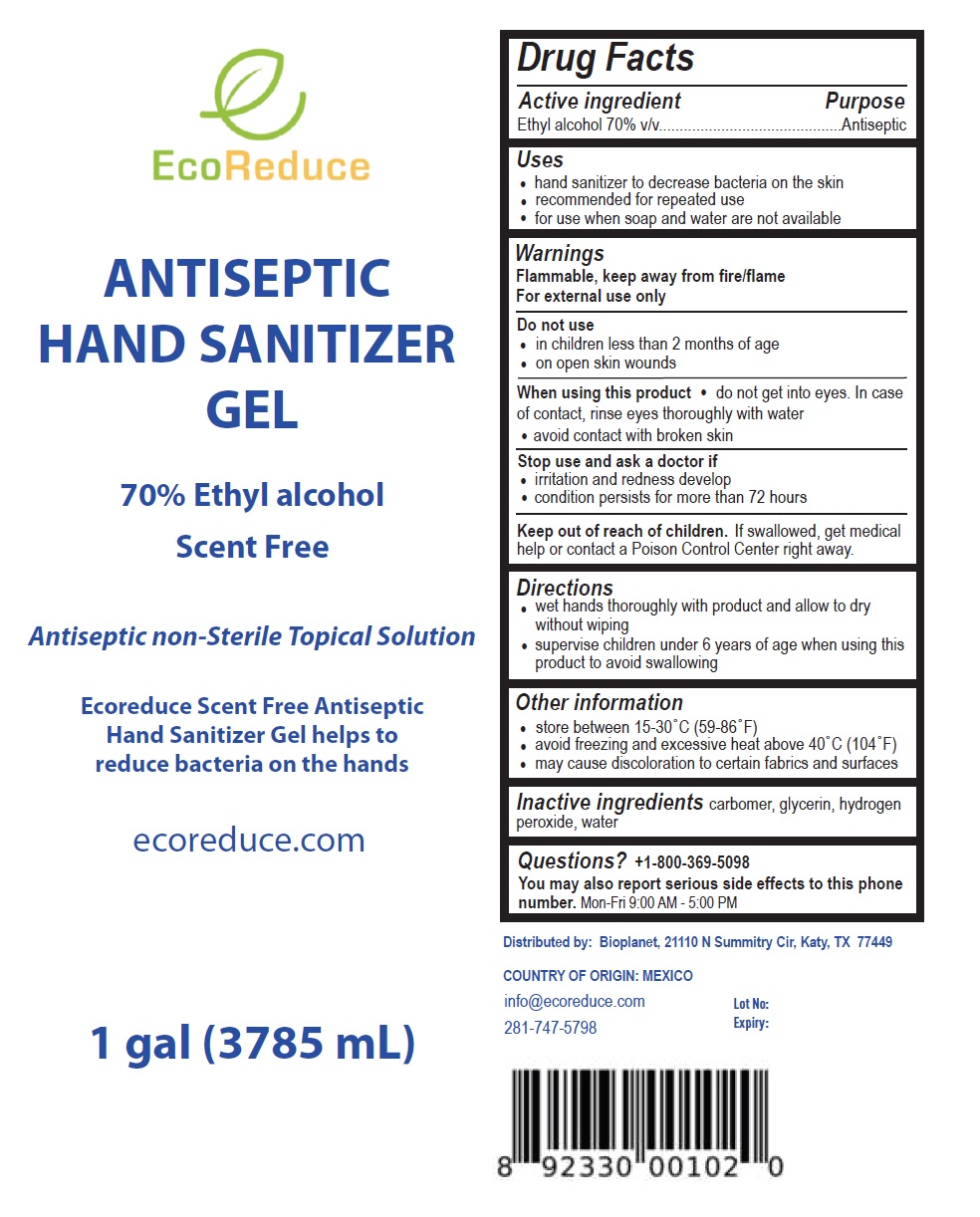 DRUG LABEL: EcoReduce ANTISEPTIC HAND SANITIZER
NDC: 80119-101 | Form: GEL
Manufacturer: Bioplanet Corp.
Category: otc | Type: HUMAN OTC DRUG LABEL
Date: 20200826

ACTIVE INGREDIENTS: ALCOHOL 70 mL/100 mL
INACTIVE INGREDIENTS: CARBOMER HOMOPOLYMER, UNSPECIFIED TYPE; GLYCERIN; HYDROGEN PEROXIDE; WATER

EcoReduce ANTISEPTIC HAND SANITIZER GEL

Active ingredient

Ethyl alcohol 70% v/v

Purpose

Antiseptic

Uses

- hand sanitizer to decrease bacteria on the skin
- recommended for repeated use
- for use when soap and water are not available

Warnings

Flammable, keep away from fire/flame

For external use only

Do not use

- in children less than 2 months of age
- on open skin wounds

When using this product • do not get into eyes. In case of contact, rinse eyes thoroughly with water

- avoid contact with broken skin

Stop use and ask a doctor if

- irritation and redness develop
- condition persists for more than 72 hours

Keep out of reach of children. If swallowed, get medical help or contact a Poison Control Center right away.

Directions

- wet hands thoroughly with product and allow to dry without wiping
- supervise children under 6 years of age when using this product to avoid swallowing

Other information

- store between 15-30°C (59-86°F)
- avoid freezing and excessive heat above 40°C (104°F)
- may cause discoloration to certain fabrics and surfaces

Inactive ingredients

carbomer, glycerin, hydrogen peroxide, water

Questions?

+1-800-369-5098

You may also report serious side effects to this phone number.

Mon-Fri 9:00 AM - 5:00 PM

Scent Free

Antiseptic non-Sterile Topical Solution

Ecoreduce Scent Free Antiseptic Hand Sanitizer Gel helps to reduce bacteria on the hands

ecoreduce.com

Distributed by: Bioplanet, 21110 N Summitry Cir, Katy, TX 77449

COUNTRY OF ORIGIN: MEXICO

info@ecoreduce.com

281-747-5798